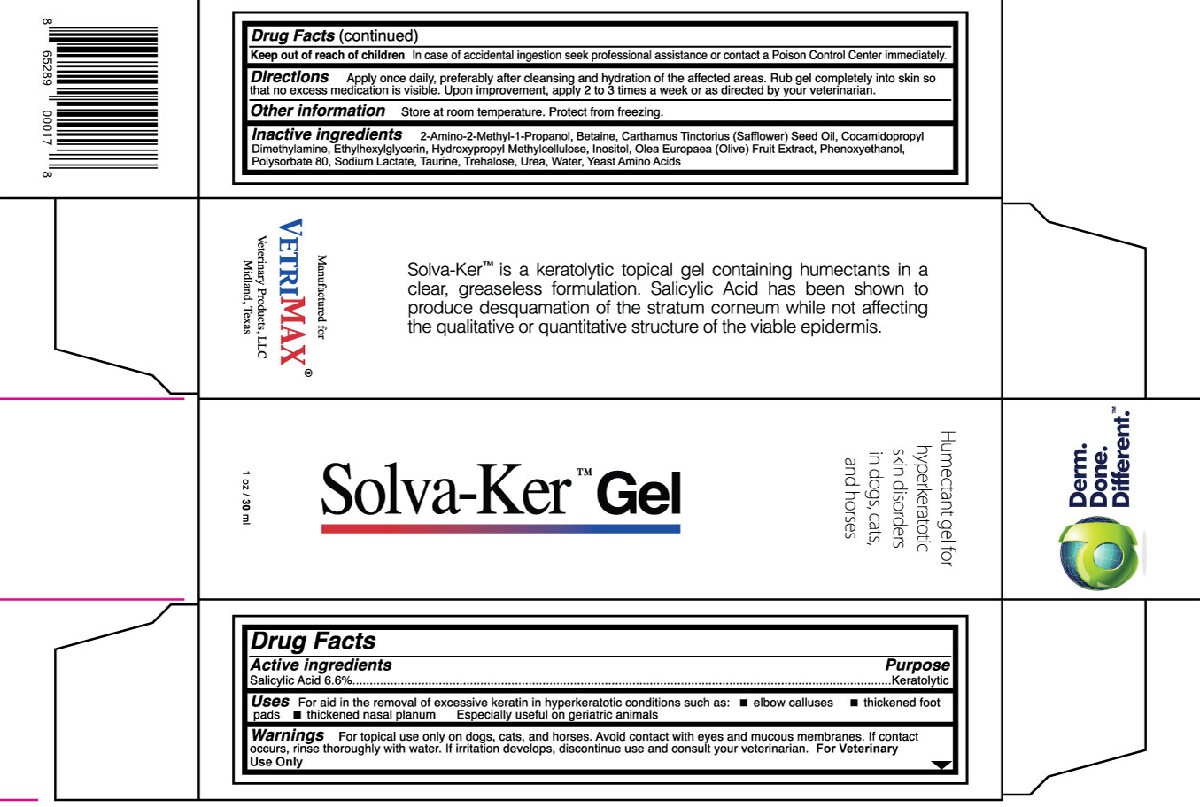 DRUG LABEL: Solva-Ker
NDC: 86030-066 | Form: GEL
Manufacturer: VetriMax Veterinary Products, LLC
Category: animal | Type: OTC ANIMAL DRUG LABEL
Date: 20251002

ACTIVE INGREDIENTS: SALICYLIC ACID 66 mg/1 mL
INACTIVE INGREDIENTS: WATER; HYPROMELLOSE, UNSPECIFIED; AMINOMETHYLPROPANOL; UREA; YEAST, UNSPECIFIED; TREHALOSE; INOSITOL; TAURINE; BETAINE; SODIUM LACTATE; PHENOXYETHANOL; ETHYLHEXYLGLYCERIN; POLYSORBATE 80; OLIVE OIL; SAFFLOWER OIL; COCAMIDOPROPYL DIMETHYLAMINE

Solva-Ker Gel

Drug Facts

Active Ingredients

Salicylic Acid 6.6%

Uses

For aid in the removal of excessive keratin in hyperkeratotic conditions such as:

- elbow calluses
- thickened foot pads
- thickened nasal planum

Especially useful on geriatric animals

Warnings

For topical use only on dogs, cats, and horses. Avoid contact with eyes and mucous membranes. If contact occurs, rinse thoroughly with water. If irritation develops, discontinue use and consult your veterinarian. For Veterinary Use Only

Keep out of reach of children

In case of accidental ingestion seek professional assistance or contact a Poison Control Center immediately.

Directions

Apply once daily, preferably after cleansing and hydration of the affected areas. Rub gel completely into skin so that no excess medication is visible. Upon improvement, apply 2 to 3 times a week or as directed by your veterinarian.

Other information

Store at room temperature. Protect from freezing.

Inactive ingredients

2-Amino-2-Methyl-1-Propanol, Betaine, Carthamus Tinctorius (Safflower) Seed Oil, Cocamidopropyl Dimethylamine, Ethylhexylglycerin, Hydroxypropyl Methylcellulose, Inositol, Olea Europaea (Olive) Fruit Extract, Phenoxyethanol, Polysorbate 80, Sodium Lactate, Taurine, Trehalose, Urea, Water, Yeast Amino Acid

PACKAGE LABEL

Solva-Ker Gel

1 oz / 30 ml